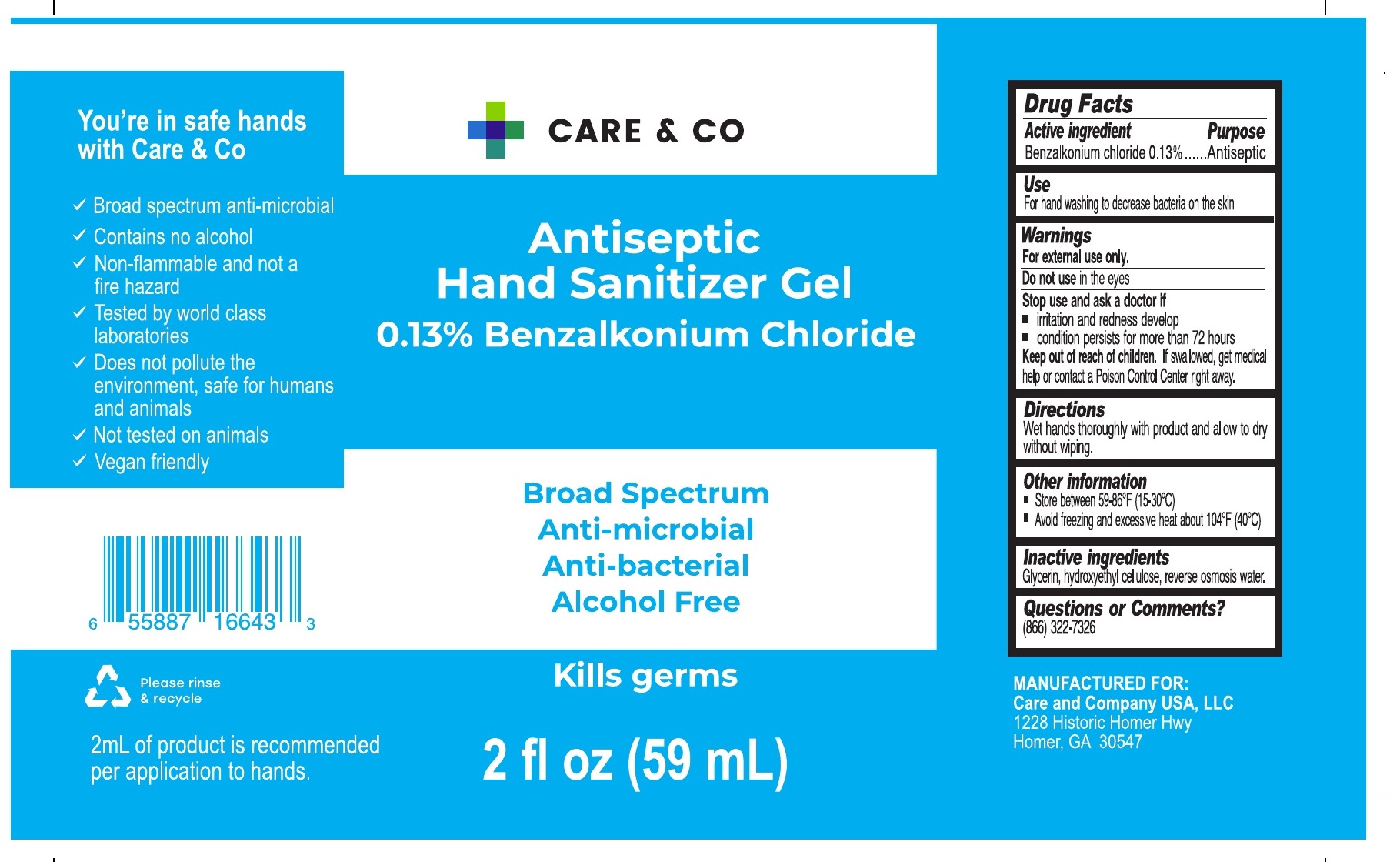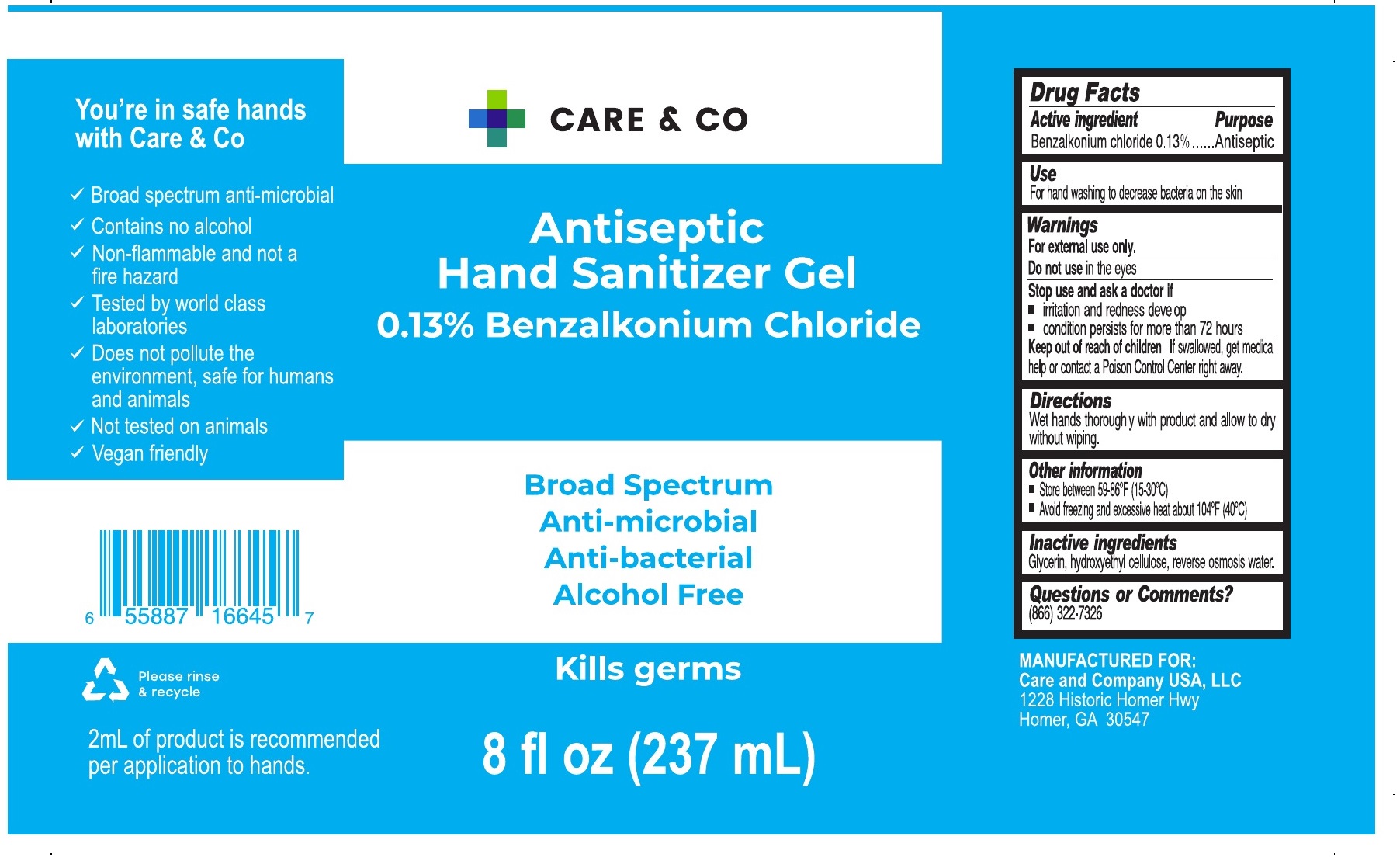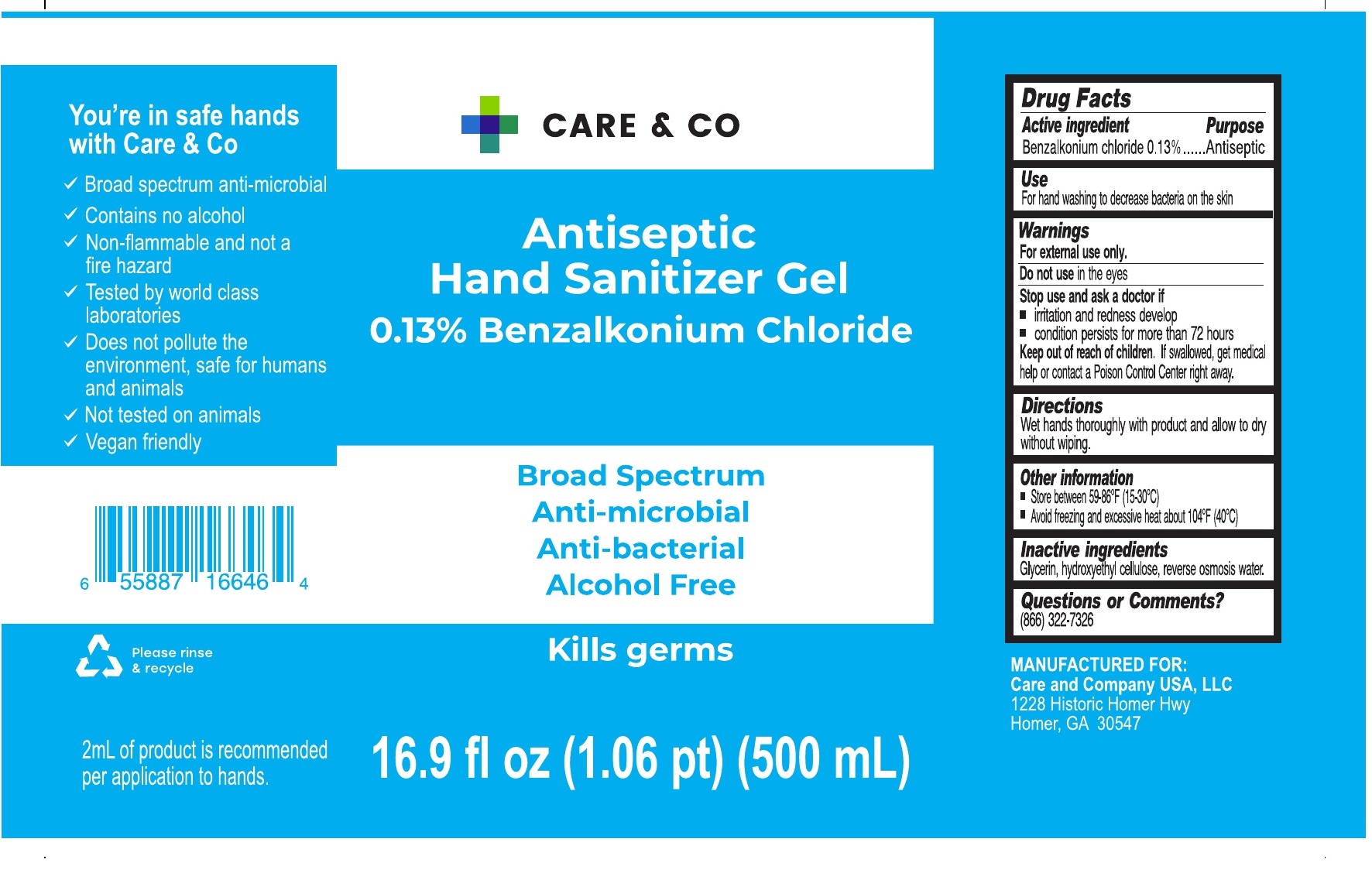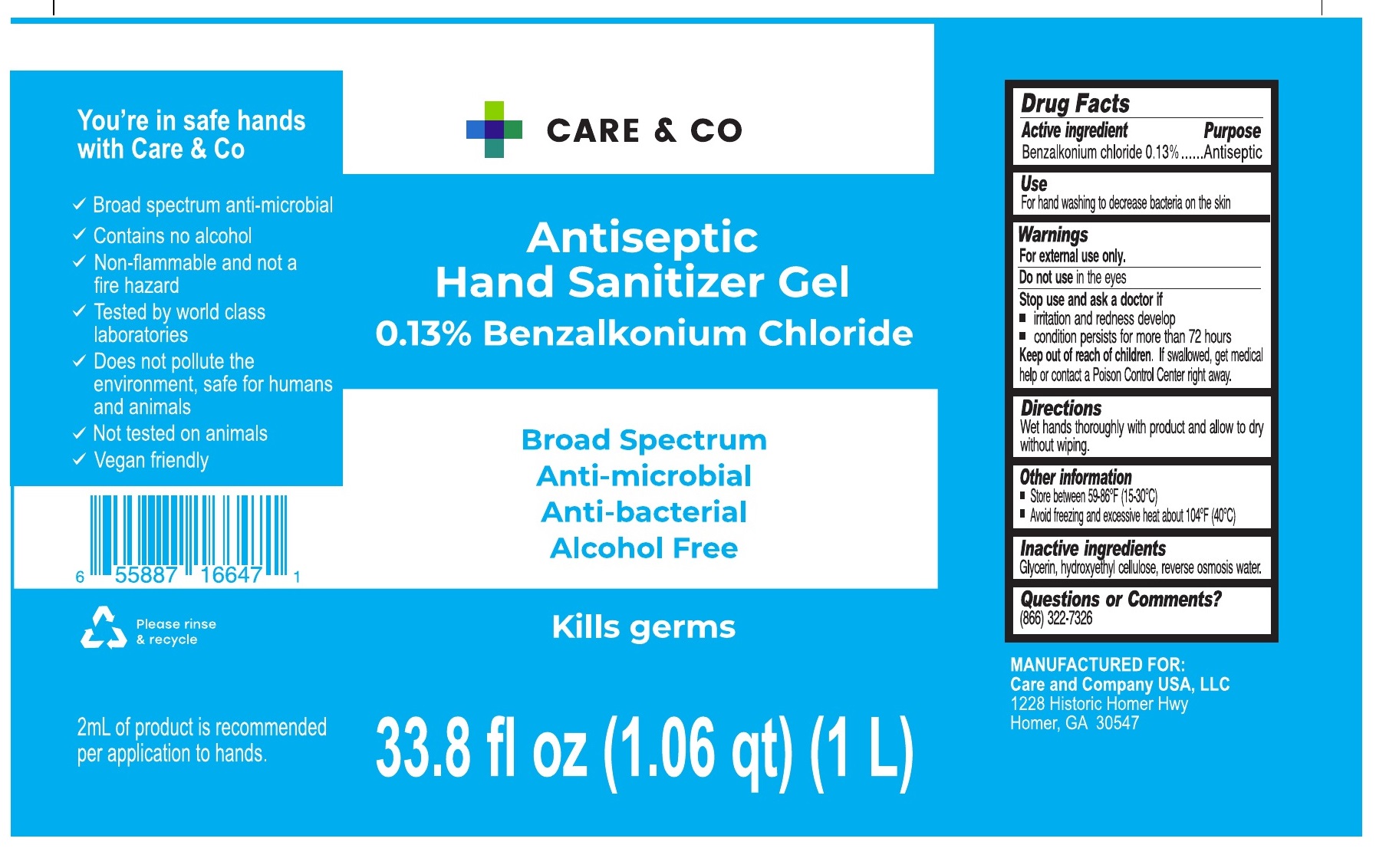 DRUG LABEL: Care and Co Hand Sanitizer
NDC: 80755-000 | Form: GEL
Manufacturer: CARE AND COMPANY USA. LLC
Category: otc | Type: HUMAN OTC DRUG LABEL
Date: 20210203

ACTIVE INGREDIENTS: BENZALKONIUM CHLORIDE 1.3 mg/1 mL
INACTIVE INGREDIENTS: HYDROXYETHYL CELLULOSE, UNSPECIFIED; WATER; GLYCERIN

Care & Co Hand Sanitizer Gel

Active ingredient

Benzalkonium chloride 0.13%

Purpose

Antiseptic

Use

For hand washing to decrease bacteria on the skin

Warnings

For external use only.

Do not use

in the eyes

Stop use and ask a doctor if

- irritation and redness develop
- condition persists for more than 72 hours

Keep out of reach of children.

If swallowed, get medical help or contact a Poison Control Center right away.

Directions

Wet hands thoroughly with product and allow to dry without wiping.

Other information

- Store between 59-86°F (15-30°C)
- Avoid freezing and excessive heat above 104°F (40°C)

Inactive ingredients

Glycerin, hydroxyethyl cellulose, reverse osmosis water.

Questions or Comments?

(866) 322-7326